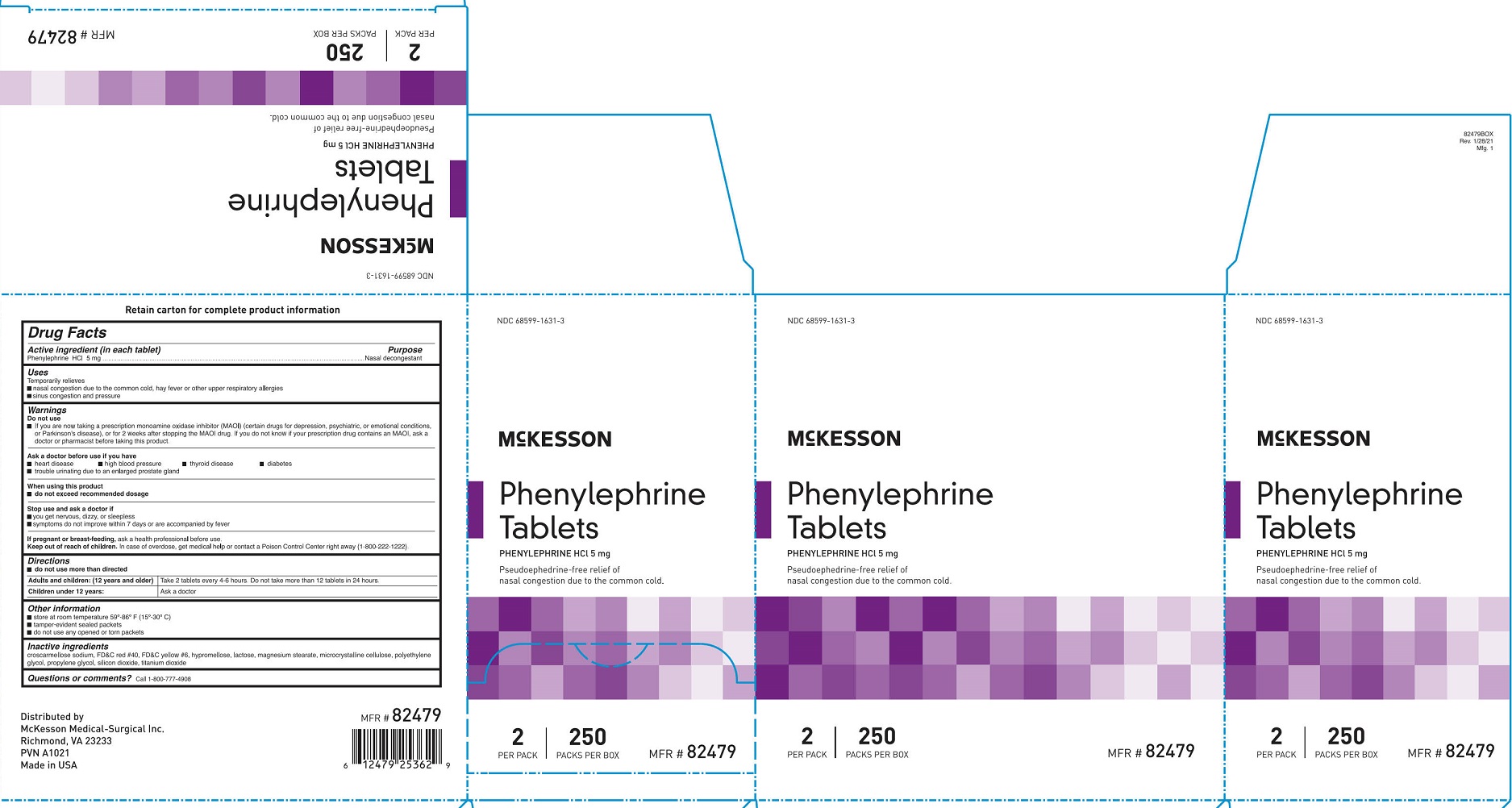 DRUG LABEL: McKesson Phenylephrine HCl
NDC: 68599-1631 | Form: TABLET, FILM COATED
Manufacturer: McKesson Medical-Surgical
Category: otc | Type: HUMAN OTC DRUG LABEL
Date: 20241108

ACTIVE INGREDIENTS: PHENYLEPHRINE HYDROCHLORIDE 5 mg/1 1
INACTIVE INGREDIENTS: FD&C YELLOW NO. 6; CROSCARMELLOSE SODIUM; FD&C RED NO. 40; HYPROMELLOSE, UNSPECIFIED; PROPYLENE GLYCOL; MAGNESIUM STEARATE; CELLULOSE, MICROCRYSTALLINE; POLYETHYLENE GLYCOL, UNSPECIFIED; LACTOSE, UNSPECIFIED FORM; SILICON DIOXIDE; TITANIUM DIOXIDE

McKesson Phenylephrine HCl

Drug Facts

Active ingredient (in each tablet)

Phenylephrine HCl 5mg

Purpose

Nasal decongestant

Uses

Temporarily relieves

- nasal congestion due to the common cold, hay fever or other upper respiratory allergies
- sinus congestion and pressure

Warnings

Do not use

- If you are now taking a prescription monoamine oxidase inhibitor (MAOI) (certain drugs for depression, psychiatric, or emotional conditions, or Parkinson's disease), or for 2 weeks after stopping the MAOI drug. If you do not know if your prescription drug contains an MAOI, ask a doctor or pharmacist before taking this product.

Ask a doctor before use if you have

- heart disease
- high blood pressure
- thyroid disease
- diabetes
- trouble urinating due to an enlarged prostate gland

When using this product

- do not exceed recommended dosage

Stop use and ask a doctor if

- you get nervous, dizzy, or sleepless
- symptoms do not improve within 7 days or are accompanied by fever

PREGNANCY OR BREAST FEEDING

If pregnant or breast-feeding, ask a health professional before use.

Keep out of reach of children. In case of overdose, get medical help or contact a Poison Control Center right away (1-800-222-1222).

Directions

- do not use more than directed

Adults and children: (12 years and older)

Take 2 tablets every 4-6 hours. Do not take more than 12 tablets in 24 hours.

Children under 12 years:

Ask a doctor

Other information

- store at room temperature 59º-86º F (15º-30º C).
- tamper evident sealed packets.
- do not use any opened or torn packets

Inactive ingredients

croscarmellose sodium, FD&C red #40, FD&C yellow #6, hypromellose, lactose, magnesium stearate, microcrystalline cellulose, polyethylene glycol, propylene glycol, silicon dioxide, titanium dioxide

Questions or comments? Call 1-800-777-4908

PACKAGE LABEL

McKesson

Phenylephrine Tablets

NDC 68599-1631-3

Phenylephrine HCl 5 mg

Pseudoephrine-free relief of nasal congestion due to the common cold.

2 Per Pack

250 Packs Per Box

MFR # 82479